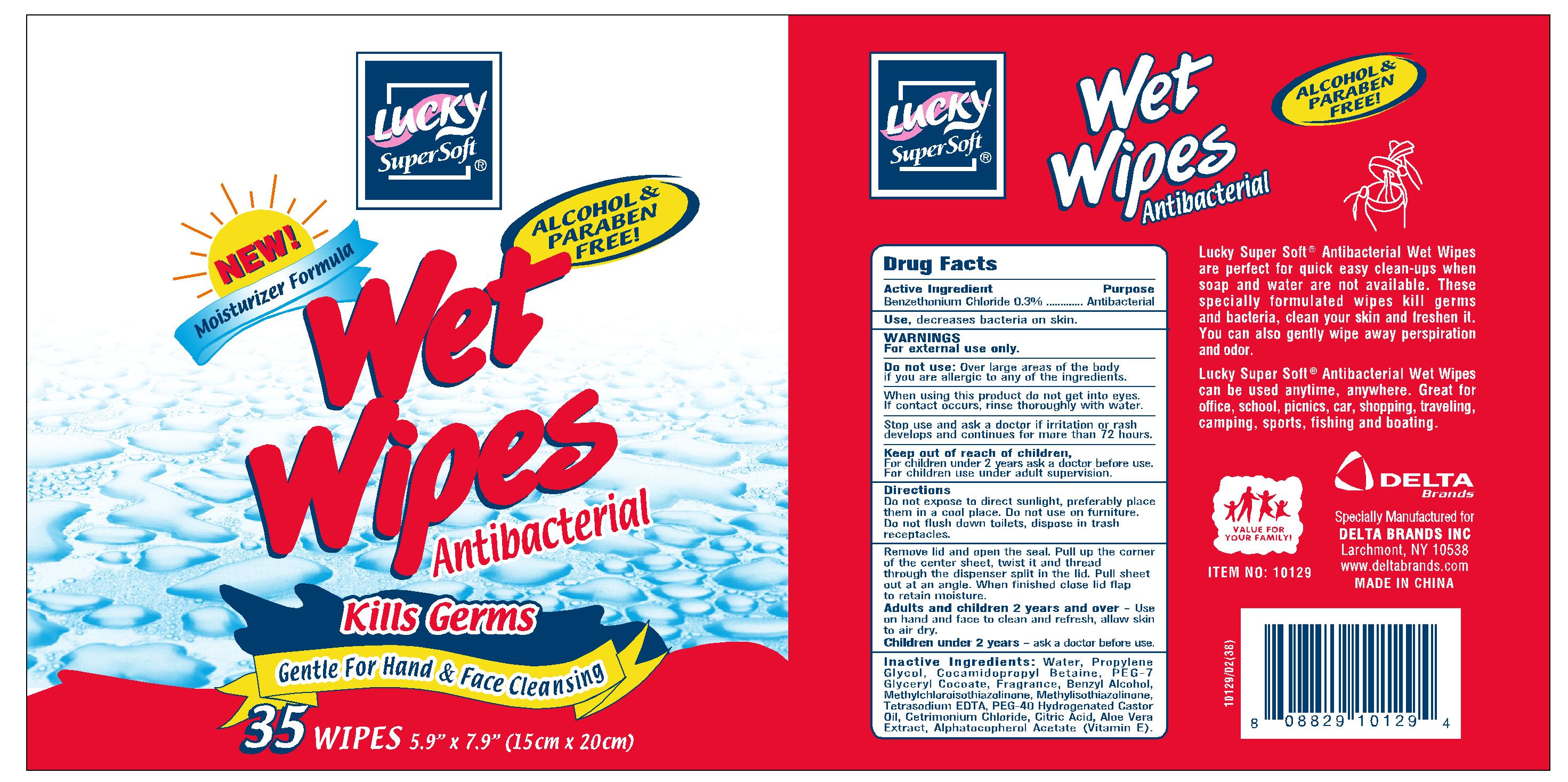 DRUG LABEL: Wet Wipes
NDC: 20276-432 | Form: SWAB
Manufacturer: Delta Brands, Inc
Category: otc | Type: HUMAN OTC DRUG LABEL
Date: 20110819

ACTIVE INGREDIENTS: BENZETHONIUM CHLORIDE 0.3 mL/1 1
INACTIVE INGREDIENTS: WATER; PROPYLENE GLYCOL; COCAMIDOPROPYL BETAINE; BENZYL ALCOHOL; METHYLCHLOROISOTHIAZOLINONE; METHYLISOTHIAZOLINONE; EDETATE SODIUM; CETRIMONIUM CHLORIDE; CITRIC ACID MONOHYDRATE; ALOE VERA LEAF; ALPHA-TOCOPHEROL ACETATE

Drug Facts

Active Ingredient

Benzethonium Chloride 0.3%

Purpose

Antibacterial

Uses

decreases bacteria on the skin

Warnings

For external use only

Do not use

Over large areas of the body if you are allergic to any of the ingredients

When using this product do not get into eyes.
If contact occurs, rinse thoroughly with water.

Stop use

Stop use and ask a doctor if irritation or rash develops and continues for more than 72 hours

Keep out of reach of children, for children under 2 years ask a doctor before use. for children use under adult supervision

Directions

Do not expose to direct sunlight, preferably place them in a cool place. Do not use on furniture. Do not flush down toilets, dispose in trash receptacles. Remove lid and open the seal Pull up the corner of the center sheet, twist it and thread through the dispenser split in the lid. Pull sheet out at an angle. When finished close lid flap to retain moisture. Adults and children 2 years and over - Use on hand and face to clean and refresh, allow skin to air dry. Children under 2 years of age - ask a doctor before use

Inactive Ingredients

Water, Propylene Glycol, Cocamidopropyl Betaine, PEG-7 Glyceryl Cocoate, Fragrance, Benzyl Alcohol, Methylchloroisothiazolinine, Methylisothiazolinone, Tetrasodium EDTA, PEG-40 Hydrogenated Castor Oil, Cetrimonium Chloride, Citric Acid, Aloe Vera Extract, Alphatocopherol Acetate (Vitamin E)

Package Label